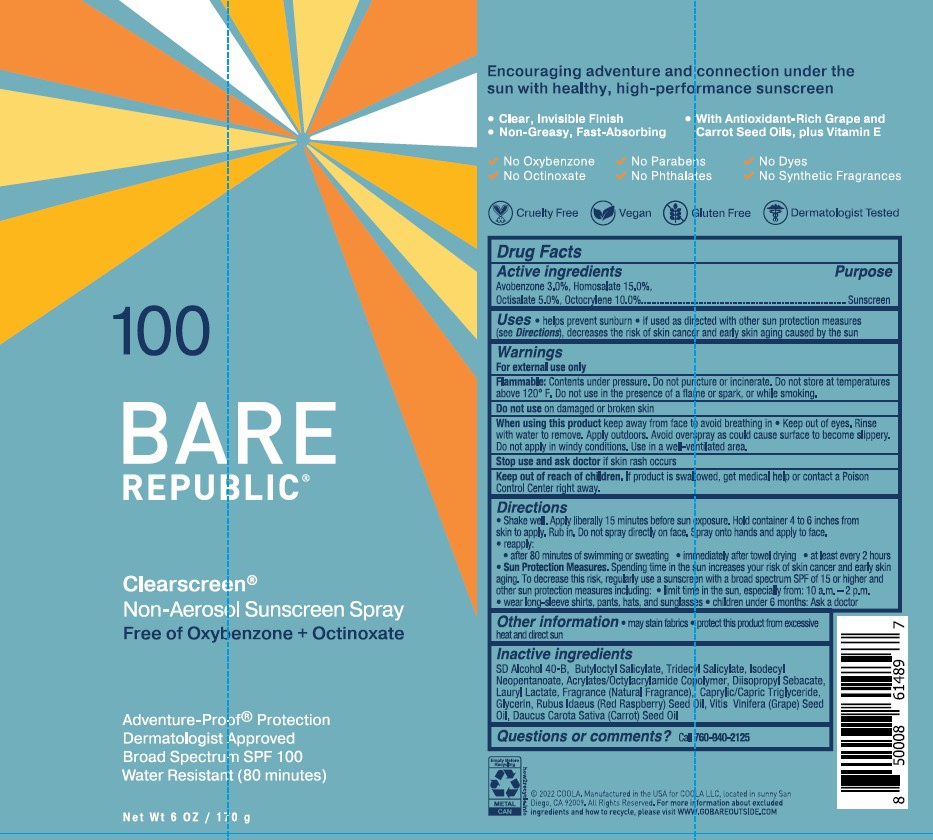 DRUG LABEL: COOLA BARE REPUBLIC CLEARSCREEN SUNSCREEN SPF100
NDC: 79753-023 | Form: SPRAY
Manufacturer: COOLA, LLC
Category: otc | Type: HUMAN OTC DRUG LABEL
Date: 20251215

ACTIVE INGREDIENTS: AVOBENZONE 30 mg/1 g; HOMOSALATE 150 mg/1 g; OCTISALATE 50 mg/1 g; OCTOCRYLENE 100 mg/1 g
INACTIVE INGREDIENTS: TRIDECYL SALICYLATE; BUTYLOCTYL SALICYLATE; GLYCERIN; ACRYLATE/ISOBUTYL METHACRYLATE/N-TERT-OCTYLACRYLAMIDE COPOLYMER (75000 MW); ISODECYL NEOPENTANOATE; ALCOHOL; MEDIUM-CHAIN TRIGLYCERIDES; RASPBERRY SEED OIL; LAURYL LACTATE; DIISOPROPYL SEBACATE; GRAPE SEED OIL; CARROT SEED OIL

COOLA BARE REPUBLIC CLEARSCREEN SPF100 NON-AEROSOL SUNSCREEN SPRAY

Active ingredients

Avobenzone 3.0%, Homosalate 15.0%, Octisalate 5.0%, Octocrylene 10.0%

Purpose

Sunscreen

Uses

- helps prevent sunburn
- if used as directed with other sun protection measures (see Directions), decreases the risk of skin cancer and early skin aging caused by the sun

Warnings

For external use only

FLAMMABLE:

• do not use near heat, flame or while smoking
• avoid long term storage above 104°F (40°C)

Do not use

- on damaged or broken skin

When using this product

• keep out of eyes. Rinse with water to remove. • do not puncture or incinerate. Contents under pressure. • do not store at temperatures above 120° F.

Stop use and ask doctor if

- rash occurs.

Keep out of reach of children.

If product is swallowed, get medical help or contact a Poison Control Center right away.

Directions

• spray liberally and spread evenly 15 minutes before sun exposure
• hold can 4-6 inches away fromskin to apply
• do not spray into face. Spray into hand and apply to face.

- Do not apply in windy conditions

• use in well ventilated, but not windy areas
reapply:
• after 80 minutes of swimming or sweating
• immediately after towel drying
• at least every 2 hours

- children under 6 months: Ask a doctor

- Sun Protection Measures. Spending time in the sun increases your risk of skin cancer and early skin aging. To decrease this risk, regularly use a sunscreen with a Broad Spectrum SPF value of 15 or higher and other sun protection measures including:

• limit time in the sun, especially from 10 a.m. - 2 p.m.
• wear long-sleeved shirts, pants, hats, and sunglasses

Other Information

• protect the product in this container from excessive heat and direct sun
• may stain or damage some fabrics, materials or surfaces

Inactive ingredients

SD Alcohol 40-B, Butyloctyl Salicylate, Tridecyl Salicylate, Isodecyl Neopentanoate, Acrylates/Octylacrylamide Copolymer, Diisopropyl Sebacate, Lauryl Lactate, Fragrance (Natural Fragrance), Caprylic/Capric Triglyceride, Glycerin, Rubus Idaeus (Red Raspberry) Seed Oil, Vitis Vinifera (Grape) Seed Oil, Daucus Carota Sativa (Carrot) Seed Oil